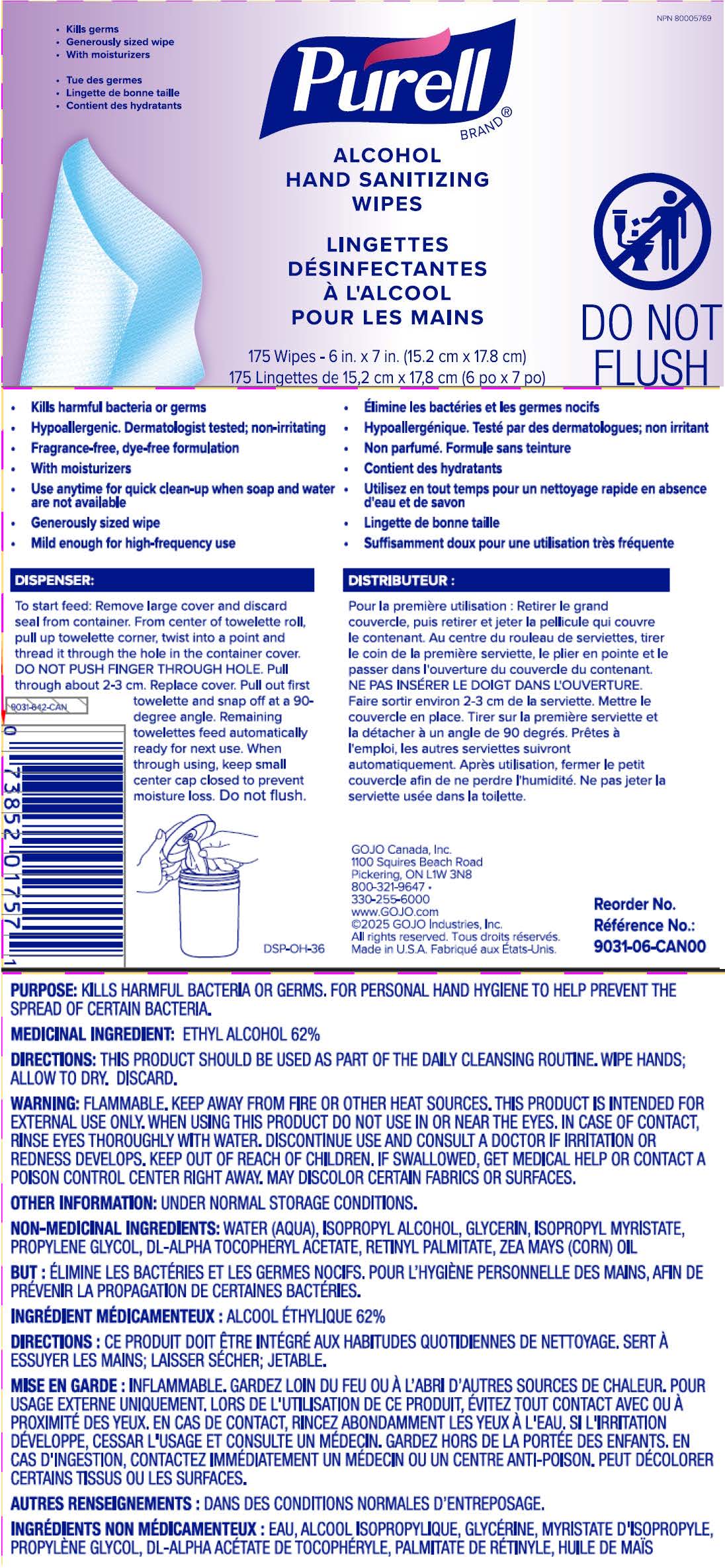 DRUG LABEL: PURELL Alcohol Hand Sanitizing Wipes
NDC: 21749-300 | Form: CLOTH
Manufacturer: GOJO Industries, Inc.
Category: otc | Type: HUMAN OTC DRUG LABEL
Date: 20251107

ACTIVE INGREDIENTS: ALCOHOL 62 mL/100 mL
INACTIVE INGREDIENTS: WATER; ISOPROPYL ALCOHOL; GLYCERIN; ISOPROPYL MYRISTATE; PROPYLENE GLYCOL; VITAMIN A PALMITATE; .ALPHA.-TOCOPHEROL ACETATE; CORN OIL

PURELL Alcohol Hand Sanitizing Wipes